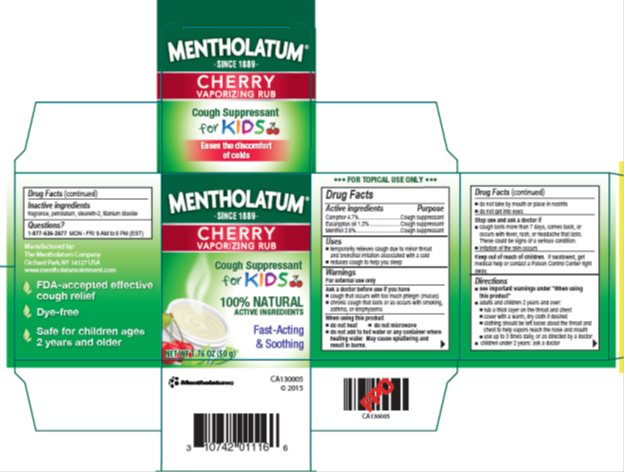 DRUG LABEL: Mentholatum Cherry Vaporizing Rub
NDC: 10742-8731 | Form: OINTMENT
Manufacturer: The Mentholatum Company
Category: otc | Type: HUMAN OTC DRUG LABEL
Date: 20241217

ACTIVE INGREDIENTS: CAMPHOR (NATURAL) 47 mg/1 g; EUCALYPTUS OIL 12 mg/1 g; MENTHOL 26 mg/1 g
INACTIVE INGREDIENTS: PETROLATUM; STEARETH-2; TITANIUM DIOXIDE

Drug Facts - Mentholatum Cherry Vaporizing Rub

Active ingredients

Camphor 4.7%

Eucalyptus oil 1.2%

Menthol 2.6%

Purpose

Camphor - Cough suppressant

Eucalyptus oil - Cough suppressant

Menthol, natural - Cough suppressant

Uses

- temporarily relieves cough due to minor throat and bronchial irritation associated with a cold
- reduces cough to help you sleep

Warnings

For external use only

Ask a doctor before use if you have

- cough that occurs with too much phlegm (mucus)
- chronic cough that lasts or as occurs with smoking, asthma, or emphysema

When using this product

- do not heat
- do not microwave
- do not add to hot water or any container where heating water. May cause splattering and result in burns.
- do not take by mouth or place in nostrils
- do not get into eyes

Stop use and ask a doctor if

- cough lasts more than 7 days, comes back, or occurs with fever, rash, or headache that lasts. These could be signs of a serious condition.
- irritation of the skin occurs

Keep out of reach of children.

If swallowed, get medical help or contact a Poison Control Center right away.

Directions

- see important warnings under "When using this product"
- adults and children 2 years and over:
- rub a thick layer on throat and chest
- cover with a warm, dry cloth if desired
- clothing should be left loose about the throat and chest to help vapors reach the nose and mouth
- use up to 3 times daily, or as directed by a doctor
- children under 2 years: ask a doctor

Inactive ingredients

fragrance, petrolatum, steareth-2, titanium dioxide

Questions?

Toll free 1-877-636-2677 MON-FRI 9AM to 5PM